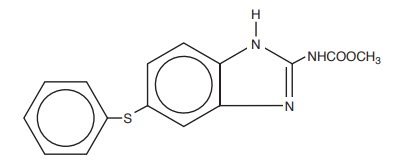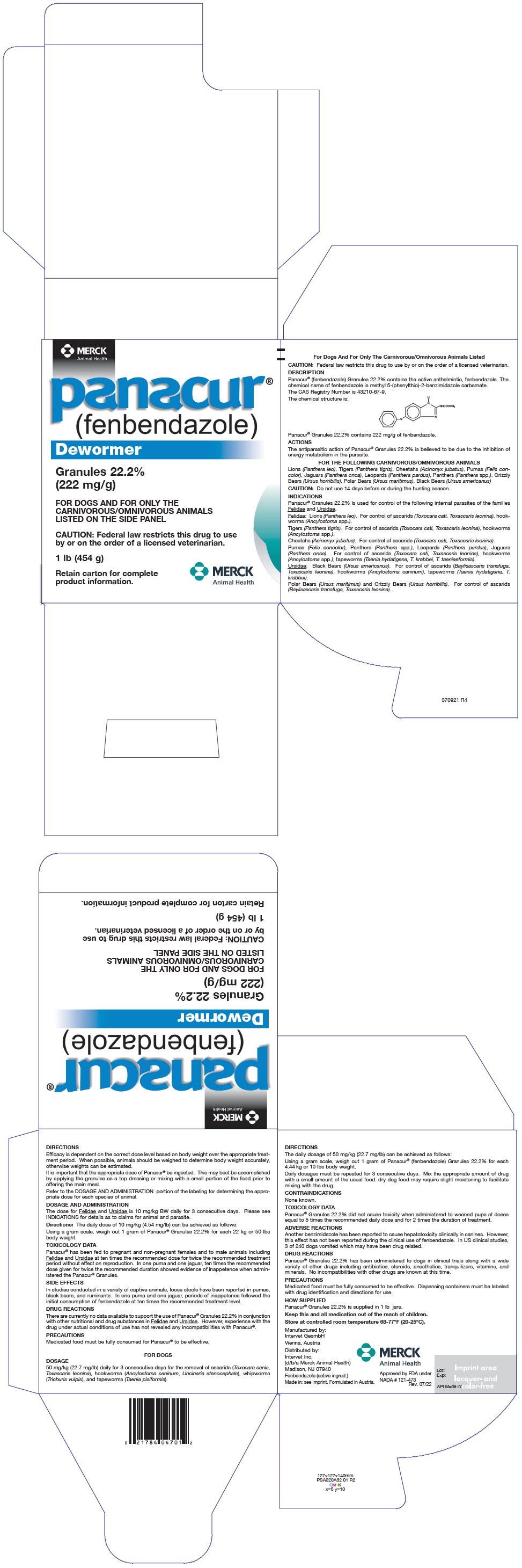 DRUG LABEL: Panacur
NDC: 57926-474 | Form: GRANULE
Manufacturer: Merck Sharp & Dohme Corp.
Category: animal | Type: PRESCRIPTION ANIMAL DRUG LABEL
Date: 20241104

ACTIVE INGREDIENTS: FENBENDAZOLE 222 mg/1 g

panacur®
(fenbendazole)

CAUTION: Federal law restricts this drug to use by or on the order of a licensed veterinarian.

DESCRIPTION

Panacur® (fenbendazole) Granules 22.2% contains the active anthelmintic, fenbendazole. The chemical name of fenbendazole is methyl 5-(phenylthio)-2-benzimidazole carbamate.

The CAS Registry Number is 43210-67-9.

The chemical structure is:

Panacur® Granules 22.2% contains 222 mg/g of fenbendazole.

ACTIONS

The antiparasitic action of Panacur® Granules 22.2% is believed to be due to the inhibition of energy metabolism in the parasite.

FOR THE FOLLOWING CARNIVOROUS/OMNIVOROUS ANIMALS

Lions (Panthera leo), Tigers (Panthera tigris), Cheetahs (Acinonyx jubatus), Pumas (Felis concolor), Jaguars (Panthera onca), Leopards (Panthera pardus), Panthers (Panthera spp.), Grizzly Bears (Ursus horribilis), Polar Bears (Ursus maritimus), Black Bears (Ursus americanus)

CAUTION: Do not use 14 days before or during the hunting season.

INDICATIONS

Panacur® Granules 22.2% is used for control of the following internal parasites of the families Felidae and Ursidae.

Felidae: Lions (Panthera leo). For control of ascarids (Toxocara cati, Toxascaris leonina), hookworms (Ancylostoma spp.).

Tigers (Panthera tigris). For control of ascarids (Toxocara cati, Toxascaris leonina), hookworms (Ancylostoma spp.).

Cheetahs (Acinonyx jubatus). For control of ascarids (Toxocara cati, Toxascaris leonina).

Pumas (Felis concolor), Panthers (Panthera spp.), Leopards (Panthera pardus), Jaguars (Panthera onca). For control of ascarids (Toxocara cati, Toxascaris leonina), hookworms (Ancylostoma spp.), tapeworms (Taenia hydatigena, T. krabbei, T. taeniaeformis).

Ursidae: Black Bears (Ursus americanus). For control of ascarids (Baylisascaris transfuga, Toxascaris leonina), hookworms (Ancylostoma caninum), tapeworms (Taenia hydatigena, T. krabbei).

Polar Bears (Ursus maritimus) and Grizzly Bears (Ursus horribilis). For control of ascarids (Baylisascaris transfuga, Toxascaris leonina).

DIRECTIONS

Efficacy is dependent on the correct dose level based on body weight over the appropriate treatment period. When possible, animals should be weighed to determine body weight accurately, otherwise weights can be estimated.

It is important that the appropriate dose of Panacur® be ingested. This may best be accomplished by applying the granules as a top dressing or mixing with a small portion of the food prior to offering the main meal.

Refer to the DOSAGE AND ADMINISTRATION portion of the labeling for determining the appropriate dose for each species of animal.

DOSAGE AND ADMINISTRATION

The dose for Felidae and Ursidae is 10 mg/kg BW daily for 3 consecutive days. Please see INDICATIONS for details as to claims for animal and parasite.

Directions: The daily dose of 10 mg/kg (4.54 mg/lb) can be achieved as follows:

Using a gram scale, weigh out 1 gram of Panacur® Granules 22.2% for each 22 kg or 50 lbs body weight.

TOXICOLOGY DATA

Panacur® has been fed to pregnant and non-pregnant females and to male animals including Felidae and Ursidae at ten times the recommended dose for twice the recommended treatment period without effect on reproduction. In one puma and one jaguar, ten times the recommended dose given for twice the recommended duration showed evidence of inappetence when administered the Panacur® Granules.

SIDE EFFECTS

In studies conducted in a variety of captive animals, loose stools have been reported in pumas, black bears, and ruminants. In one puma and one jaguar, periods of inappetence followed the initial consumption of fenbendazole at ten times the recommended treatment level.

DRUG REACTIONS

There are currently no data available to support the use of Panacur® Granules 22.2% in conjunction with other nutritional and drug substances in Felidae and Ursidae. However, experience with the drug under actual conditions of use has not revealed any incompatibilities with Panacur®.

PRECAUTIONS

Medicated food must be fully consumed for Panacur® to be effective.

DOSAGE

50 mg/kg (22.7 mg/lb) daily for 3 consecutive days for the removal of ascarids (Toxocara canis, Toxascaris leonina), hookworms (Ancylostoma caninum, Uncinaria stenocephala), whipworms (Trichuris vulpis), and tapeworms (Taenia pisiformis).

DIRECTIONS

The daily dosage of 50 mg/kg (22.7 mg/lb) can be achieved as follows:

Using a gram scale, weigh out 1 gram of Panacur® (fenbendazole) Granules 22.2% for each 4.44 kg or 10 lbs body weight.

Daily dosages must be repeated for 3 consecutive days. Mix the appropriate amount of drug with a small amount of the usual food: dry dog food may require slight moistening to facilitate mixing with the drug.

CONTRAINDICATIONS

None known.

TOXICOLOGY DATA

Panacur® Granules 22.2% did not cause toxicity when administered to weaned pups at doses equal to 5 times the recommended daily dose and for 2 times the duration of treatment.

ADVERSE REACTIONS

Another benzimidazole has been reported to cause hepatotoxicity clinically in canines. However, this effect has not been reported during the clinical use of fenbendazole. In US clinical studies, 3 of 240 dogs vomited which may have been drug related.

DRUG REACTIONS

Panacur® Granules 22.2% has been administered to dogs in clinical trials along with a wide variety of other drugs including antibiotics, steroids, anesthetics, tranquilizers, vitamins, and minerals. No incompatibilities with other drugs are known at this time.

PRECAUTIONS

Medicated food must be fully consumed to be effective. Dispensing containers must be labeled with drug identification and directions for use.

HOW SUPPLIED

Panacur® Granules 22.2% is supplied in 1 lb jars.

Keep this and all medication out of the reach of children.

STORAGE AND HANDLING

Store at controlled room temperature 68-77°F (20-25°C).

Manufactured by:
Intervet GesmbH
Vienna, Austria

Distributed by:
Intervet Inc.
(d/b/a Merck Animal Health)
Madison, NJ 07940

Fenbendazole (active ingred.)
Made in: see imprint. Formulated in Austria.

Approved by FDA under
NADA # 121-473
Rev. 07/22

PRINCIPAL DISPLAY PANEL - 454 g Jar Carton

MERCK
Animal Health

panacur®
(fenbendazole)

Dewormer

Granules 22.2%
(222 mg/g)

FOR DOGS AND FOR ONLY THE
CARNIVOROUS/OMNIVOROUS ANIMALS
LISTED ON THE SIDE PANEL

CAUTION: Federal law restricts this drug to use
by or on the order of a licensed veterinarian.

1 lb (454 g)

Retain carton for complete
product information.

MERCK
Animal Health